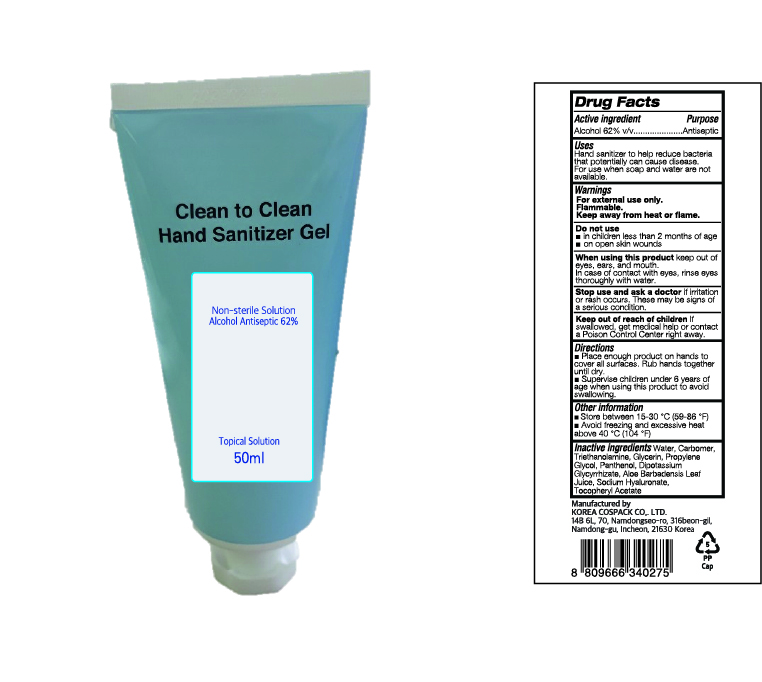 DRUG LABEL: CLEAN TO CLEAN HAND SANITIZER Gel
NDC: 74064-0562 | Form: GEL
Manufacturer: KOREA COSPACK CO.,LTD.
Category: otc | Type: HUMAN OTC DRUG LABEL
Date: 20200512

ACTIVE INGREDIENTS: ALCOHOL 31 mL/50 mL
INACTIVE INGREDIENTS: GLYCERIN; CARBOMER HOMOPOLYMER, UNSPECIFIED TYPE; WATER; PROPYLENE GLYCOL; PANTHENOL; GLYCYRRHIZINATE DIPOTASSIUM; ALOE VERA LEAF; .ALPHA.-TOCOPHEROL ACETATE; HYALURONATE SODIUM; TROLAMINE

CLEAN TO CLEAN HAND SANITIZER GEL 50 ml : 74064-0562-1